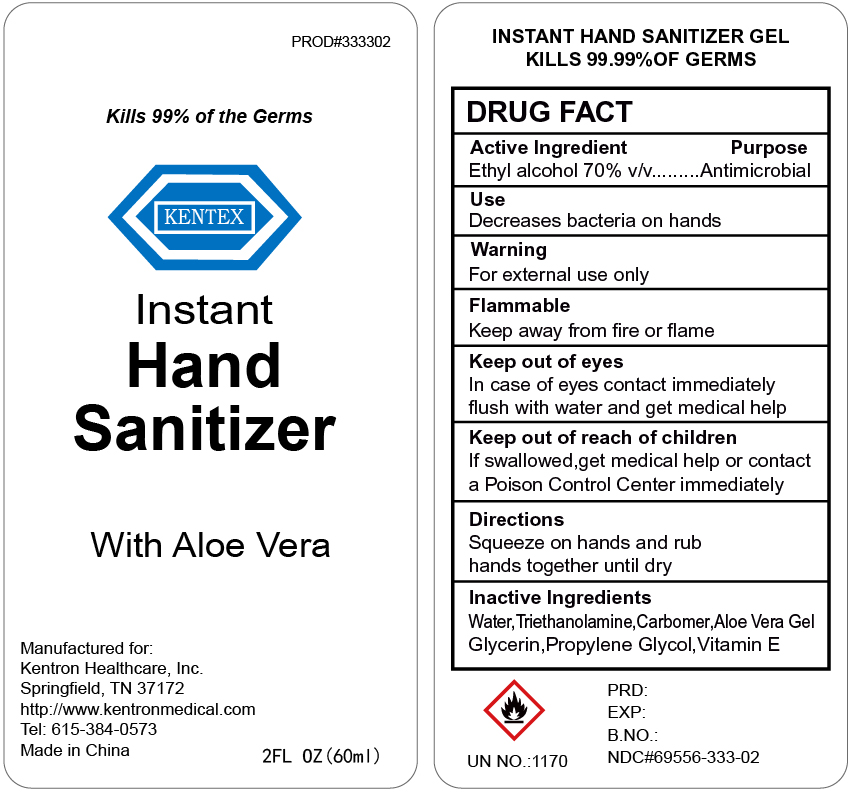 DRUG LABEL: KENTEX Instant Hand Sanitizer with Aloe Vera
NDC: 69556-333 | Form: SOLUTION
Manufacturer: Kentron Healthcare, Inc.
Category: otc | Type: HUMAN OTC DRUG LABEL
Date: 20211102

ACTIVE INGREDIENTS: ALCOHOL 70 mL/100 mL
INACTIVE INGREDIENTS: CARBOMER 940; TROLAMINE; GLYCERIN; ALOE VERA WHOLE; .ALPHA.-TOCOPHEROL ACETATE; PROPYLENE GLYCOL

ACTIVE INGREDIENT

Ethyl Alcohol 70% v/v

Purpose

Antimicrobial

Use

Decrease bacteria on hands

Warnings

For external use only

Flammable. Keep away from fire or flame

keep out of eyes. In case of eye contact, immediately flush with water and get medical help

Keep out of reach of children. If swallowed, get medical help or contact a poison control immediately

Directions

- Squeeze on hands. Rub hands together until dry

Inactive ingredients

Water, Carbomer, Triethanolamine, Glycerin, Aloe Vera Gel, Propylene Glycol, Vitamin E